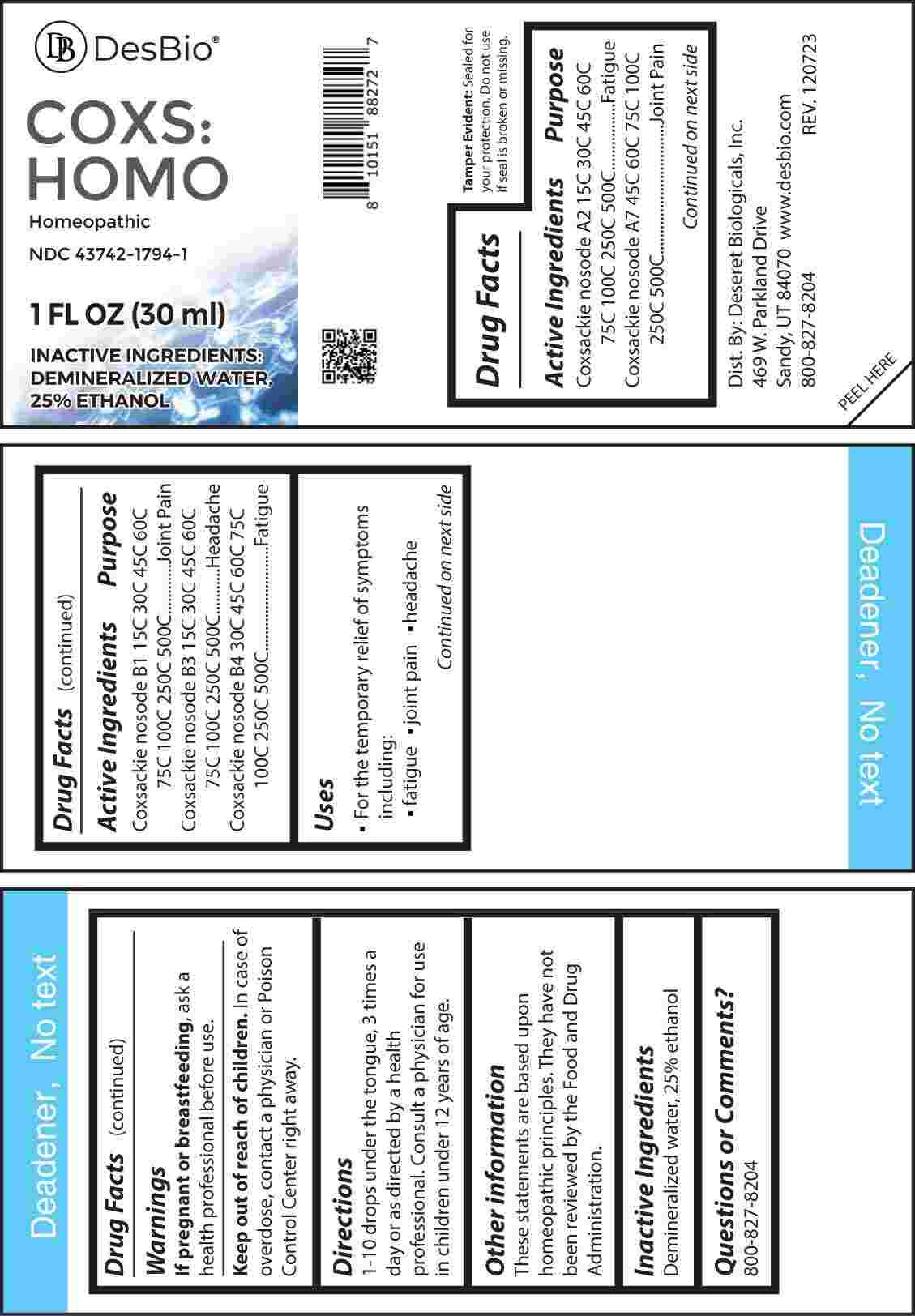 DRUG LABEL: Coxs Homo
NDC: 43742-1794 | Form: LIQUID
Manufacturer: Deseret Biologicals, Inc.
Category: homeopathic | Type: HUMAN OTC DRUG LABEL
Date: 20240319

ACTIVE INGREDIENTS: HUMAN COXSACKIEVIRUS A2 15 [hp_C]/1 mL; HUMAN COXSACKIEVIRUS B1 15 [hp_C]/1 mL; HUMAN COXSACKIEVIRUS B3 15 [hp_C]/1 mL; HUMAN COXSACKIEVIRUS B4 30 [hp_C]/1 mL; HUMAN COXSACKIEVIRUS A7 45 [hp_C]/1 mL
INACTIVE INGREDIENTS: WATER; ALCOHOL

DRUG FACTS:

ACTIVE INGREDIENTS:

Coxsackie Nosode A2 15C, 30C, 45C, 60C, 75C, 100C, 250C, 500C, Coxsackie Nosode A7 45C, 60C, 75C, 100C, 250C, 500C, Coxsackie Nosode B1 15C, 30C, 45C, 60C, 75C, 100C, 250C, 500C, Coxsackie Nosode B3 15C, 30C, 45C, 60C, 75C, 100C, 250C, 500C, Coxsackie Nosode B4 30C, 45C, 60C, 75C, 100C, 250C, 500C.

PURPOSE:

Coxsackie Nosode A2 - Fatigue, Coxsackie Nosode A7 – Joint Pain, Coxsackie Nosode B1 – Joint Pain, Coxsackie Nosode B3 - Headache, Coxsackie Nosode B4 - Fatigue

USES:

• For the temporary relief of symptoms including:

• fatigue • joint pain • headache

These statements are based upon homeopathic principles. They have not been reviewed by the Food and Drug Administration.

WARNINGS:

If pregnant or breast-feeding, ask a health professional before use.

Keep out of reach of children. In case of overdose, contact a physician or Poison Control Center right away.

Tamper Evident: Sealed for your protection. Do not use if seal is broken or missing.

KEEP OUT OF REACH OF CHILDREN:

In case of overdose, contact a physician or Poison Control Center right away.

DIRECTIONS:

1-10 drops under the tongue, 3 times a day or as directed by a health professional. Consult a physician for use in children under 12 years of age.

INACTIVE INGREDIENTS:

Demineralized water, 25% ethanol

QUESTIONS:

Dist. By: Deseret Biologicals, Inc.

469 W. Parkland Drive

Sandy, UT 84070

www.desbio.com

800-827-8204

PACKAGE LABEL DISPLAY:

Des Bio

COXS:HOMO

Homeopathic

NDC 43742-1794-1

1 FL OZ (30 ml)